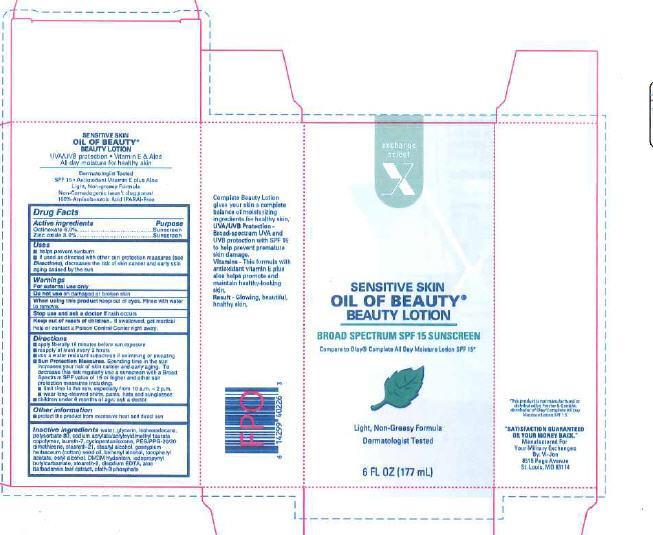 DRUG LABEL: Oil of Beauty
NDC: 55301-091 | Form: LOTION
Manufacturer: Your Military Exchange
Category: otc | Type: HUMAN OTC DRUG LABEL
Date: 20121220

ACTIVE INGREDIENTS: octinoxate 60 mg/1 mL; ZINC OXIDE 30 mg/1 mL
INACTIVE INGREDIENTS: WATER; GLYCERIN; ISOHEXADECANE; POLYSORBATE 80; SODIUM ACRYLATE/SODIUM ACRYLOYLDIMETHYLTAURATE COPOLYMER (4000000 MW); LAURETH-7; CYCLOMETHICONE 5; PEG/PPG-20/20 DIMETHICONE; STEARETH-21; STEARYL ALCOHOL; LEVANT COTTONSEED OIL; DOCOSANOL; .ALPHA.-TOCOPHEROL ACETATE; CETYL ALCOHOL; DMDM HYDANTOIN; IODOPROPYNYL BUTYLCARBAMATE; STEARETH-2; EDETATE DISODIUM; ALOE VERA LEAF; OLETH-3 PHOSPHATE

Drug Facts

Active ingredients

Octinoxate 6.0%

Zinc oxide 3.0%

Purpose

sunscreen

sunscreen

Uses

- helps prevent sunburn
- if used as directed with other sun protection measures (see Directions), decreases the risk of skin cancer and early skin aging caused by the sun

Warnings

For external use only

Do not use on damaged or broken skin

When using

When using this product keep out of eyes. Rinse with water to remove

Stop use and ask a doctor if rash occurs

Keep out of reach of children. If swallowed, get medical help or contact a Poison Control Center right away.

Directions

- apply liberally 15 minutes before sun exposure
- reapply at least every 2 hours
- use a water resistant sunscreen if swimming or sweating
- Sun Protection Measures. Spending time in the sun increases your rish of skin cancer and early skin aging. To decrease this risk, regularly ue a sunscreen with a Broad Spectrum SPF value of 15 or higher and other sun protection measures including:
- limit time in the sun, especially from 10 a.m. - 2 p.m.
- wear long-sleeved shirts, pants, hats and sunglasses
- children under 6 months of age: ask a doctor

Other information

- protect the product from excessive heat and direct sun

Inactive ingredients

Inactive Ingredientswater, glycerin, isohexadecane, polysorbate 80, sodium acrylate/acryloyldimethyl taurate copolymer, laureth-7, cyclopentasiloxane, PEG/PPG-20/20 dimethicone, steareth-21, stearyl alcohol, gossypium herbaceum (cotton) seed oil, behenyl alcohol, tocopheryl acetate, cetyl alcohol, DMDM hydantoin, iodopropynyl butylcarbamate, steareth-2, disodium EDTA, aloe barbadensis leaf extract, oleth-3 phosphate

Claims on side panel

Complete Beauty Lotion give your sking a complete balance of moisturizing ingredient for healthy skin,

UVA/UVB Protection - Broad spectrum UVA and UVB protection with SPF 15 to help prevent premature sking damage.

Vitamins - this formula with antioxidant vitamin E plus aloe helps promote and maintaind healthy-looking skin.

Result - glowing, beautiful healthy skin.

Disclaimer

This product is not manufactured or distributed by Procter + Gamble, distributor of Olay Complete All Day Moisture Lotion SPF 15

Adverse Reactions

SATISIFACTIN GUARANTEED

OR YOUR ONEY BACK.

Manufactured For

Your Military Exchanges

By: Vi-Jon

8515 Page Avenue

St. Louis, MO 63114

Prncipal display panel

SENSITIVE SKIN

OIL OF BEAUTY

BEAUTY LOTION

BROAD SPECTRUM SPF 15 SUNSCREEN

Compare to Olay Complete all Day Moistrue Lotion SPf 15

Light, Non-Greasy Formula

Dermatologist tested

6 FL OZ (177 mL)